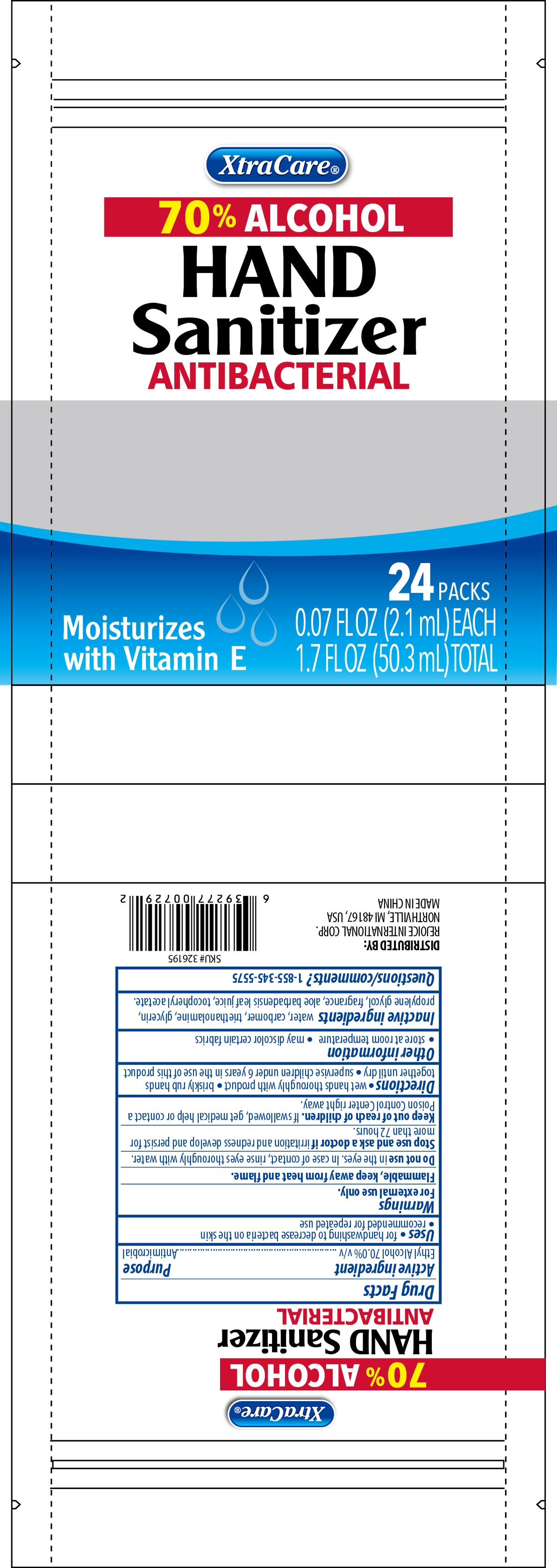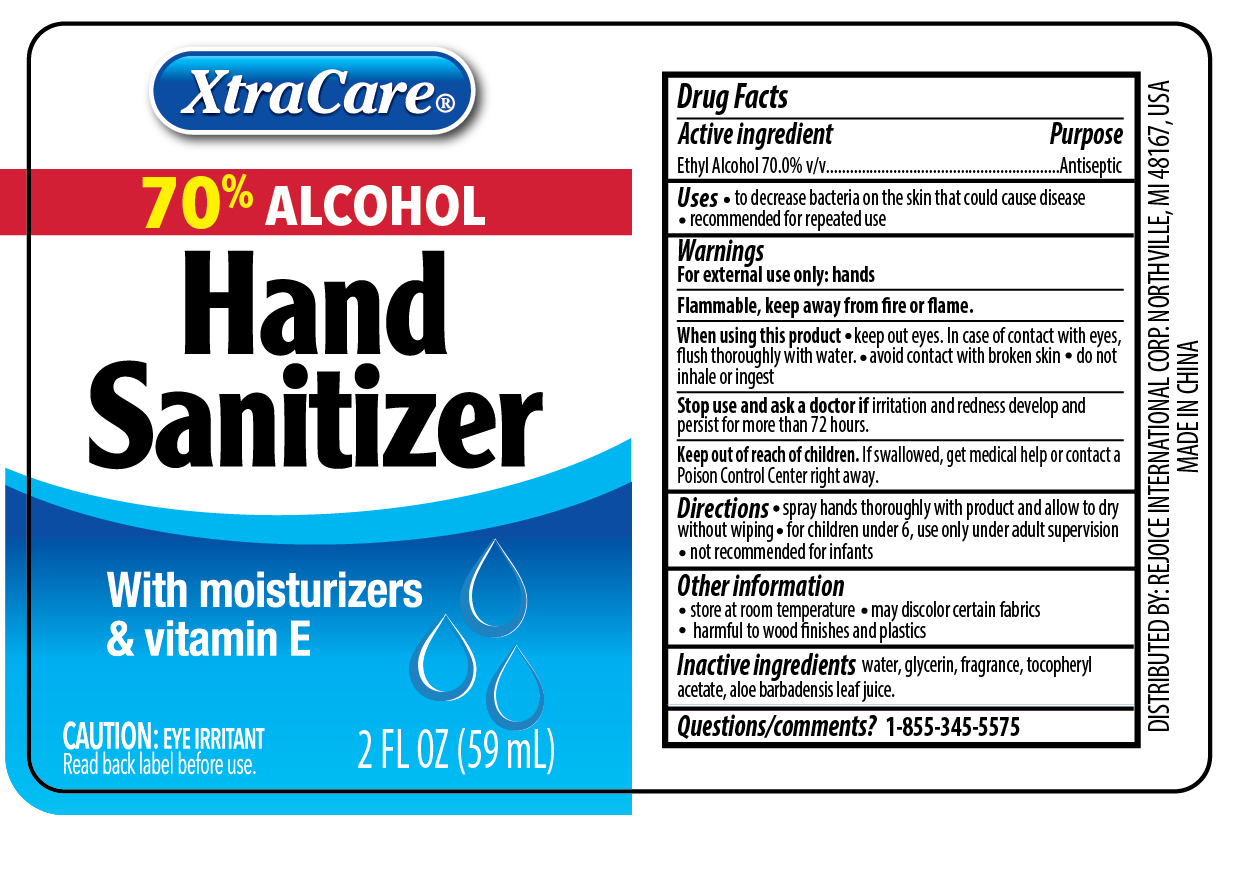 DRUG LABEL: Hand Sanitizer
NDC: 57337-132 | Form: SPRAY
Manufacturer: Ningbo Rejoice International
Category: otc | Type: HUMAN OTC DRUG LABEL
Date: 20250213

ACTIVE INGREDIENTS: ALCOHOL 70 mL/100 mL
INACTIVE INGREDIENTS: WATER; GLYCERIN; ALOE; CARBOMER HOMOPOLYMER, UNSPECIFIED TYPE; ALPHA-TOCOPHEROL ACETATE

Hand Sanitizer Spray

Active Ingredient(s)

Ethyl Alcohol 70% v/v.

Purpose

Antiseptic

Use

- for handwashing to decrease bacteria on the skin
- recommended for repeated use

Warnings

For external use only: hands. Flammable, keep away from fire or flame

Stop use and ask a doctor if irritation or rednees develp and persist for more than 72 hours.

Keep out of reach of children. If swallowed, get medical help or contact a Poison Control Center right away.

Directions

- spray hands thoroughly with product and allow to dry without wiping
- for children under 6, use only under adult supervision
- not recommended for infants

Other information

- Store at room temperature
- may discolor certain fabrics

Inactive ingredients

water, glycerin, fragrance, aloe barbadensis leaf juice, tocopheryl acetate,

QUESTIONS

1-855-345-5575

WHEN USING

- keep out eyes. In case of contact with eyes, flush thoroughly with water
- avoid contact with broken skin
- do not inhale or ingest